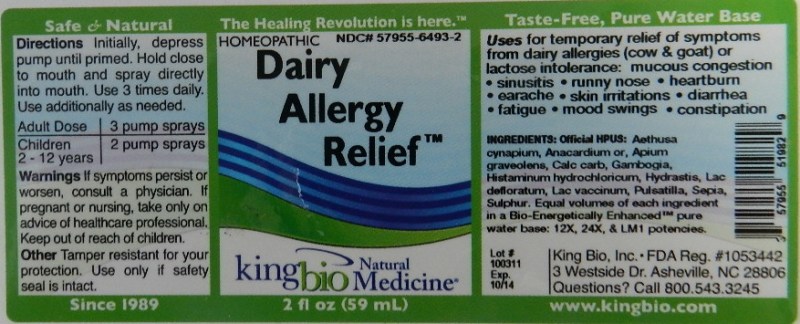 DRUG LABEL: Dairy Allergy Relief
NDC: 57955-6493 | Form: LIQUID
Manufacturer: King Bio Inc.
Category: homeopathic | Type: HUMAN OTC DRUG LABEL
Date: 20111222

ACTIVE INGREDIENTS: AETHUSA CYNAPIUM 12 [hp_X]/59 mL; SEMECARPUS ANACARDIUM JUICE 12 [hp_X]/59 mL; CELERY SEED 12 [hp_X]/59 mL; OYSTER SHELL CALCIUM CARBONATE, CRUDE 12 [hp_X]/59 mL; GAMBOGE 12 [hp_X]/59 mL; HISTAMINE DIHYDROCHLORIDE 12 [hp_X]/59 mL; GOLDENSEAL 12 [hp_X]/59 mL; SKIM MILK 12 [hp_X]/59 mL; COW MILK 12 [hp_X]/59 mL; PULSATILLA VULGARIS 12 [hp_X]/59 mL; SEPIA OFFICINALIS JUICE 12 [hp_X]/59 mL; SULFUR 12 [hp_X]/59 mL
INACTIVE INGREDIENTS: WATER

Dairy Allergy Relief

Active Ingredient's

Official HPUS: Aethusa Cynapium, Anacardium Orientale, Apium Graveolens, Calcarea Carbonica, Gambogia, Histaminum Hydrochloricum, Hydrastis Canadensis, Lac Defloratum, Lac Vaccinum, Pulsatilla. Sepia and Sulphur.

Reference image dairy.jpg

Inactive Ingredient

Equal volumes of each ingredient in a Bio-Energetically Enhanced pure water base 12X, 24X and LM1 potencies.

Reference image dairy.jpg

Indications and Usage

Uses for temporary relief of symptoms from dairy allergies (cow and goat) or lactose intolerance:

- mucous congestion
- sinusitis
- runny nose
- heartburn
- earache
- skin irritations
- diarrhea
- fatigue
- mood swings
- constipation

Reference image dairy.jpg

Dosage and Administration

Directions: Initially, depress pump until primed. Hold close to mouth and spray one dose directly into mouth. Use 3 times per day. Use additionally as needed.

Adult Dose 3 pump sprays

Children (2-12 years) 2 pump sprays

Reference image dairy.jpg

Warnings

If symptoms persist or worsen, or if pregnant or nursing, take only on advice of a healthcare professional.

Other: Tamper resistant for your protection. Use only if safety seal is intact.

Reference image dairy.jpg

Keep out of reach of children.

Reference image dairy.jpg

Purpose

Uses for temporary relief of symptoms from dairy allergies (cow and goat) or lactose intolerance: mucous congestion, sinusitis, runny nose, heartburn, earache, skin irritations, diarrhea, fatigue, mood swings and constipation.

Reference image dairy.jpg

PACKAGE LABEL

King Bio Inc.

3 Westside Drive

Asheville, NC 28806

Questions? Call 800.543.3245

www.kingbio.com

Safe and Natural

Homeopathic